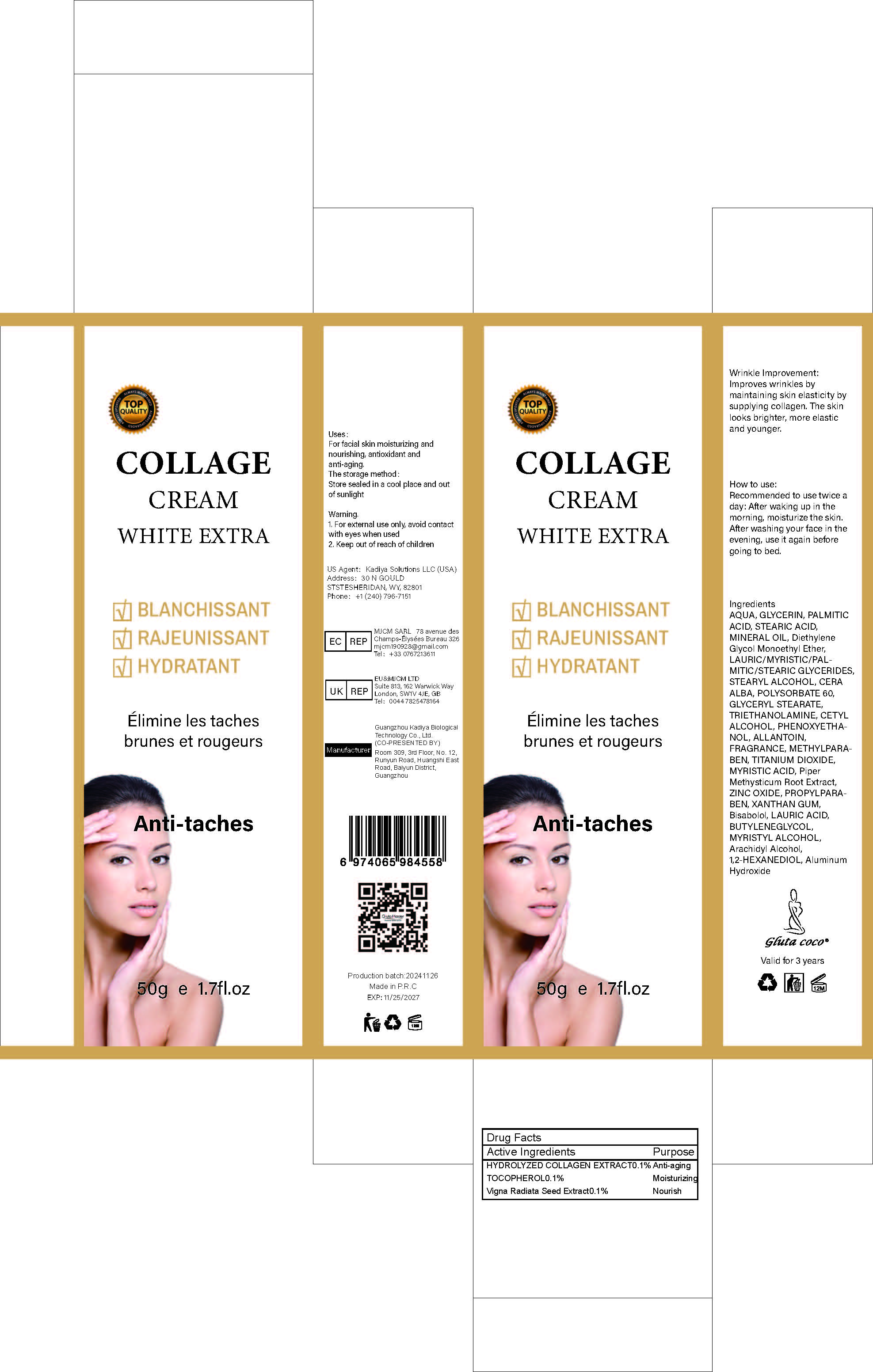 DRUG LABEL: COLLAGECREAM
NDC: 84423-072 | Form: CREAM
Manufacturer: Guangzhou Kadiya Biotechnology Co., Ltd.
Category: otc | Type: HUMAN OTC DRUG LABEL
Date: 20250217

ACTIVE INGREDIENTS: TOCOPHEROL 0.05 g/50 g; VIGNA RADIATA WHOLE 0.05 g/50 g
INACTIVE INGREDIENTS: TRIETHANOLAMINE; ALLANTOIN; WHITE WAX; PIPER METHYSTICUM ROOT; 1,3-BUTYLENEGLYCOL DIMETHACRYLATE; ARACHIDYL ALCOHOL; 1,2-HEXANEDIOL; STEARYL ALCOHOL; LAURIC ACID; MINERAL OIL; ALUMINUM HYDROXIDE; ZINC OXIDE; PROPYLPARABEN; BISABOLOL; PALMITIC ACID; MYRISTYL ALCOHOL; CETYL ALCOHOL; DIETHYLENE GLYCOL MONOETHYL ETHER; METHYLPARABEN; TITANIUM DIOXIDE; MYRISTIC ACID; PHENOXYETHANOL; XANTHAN GUM; AQUA; GLYCERIN; STEARIC ACID; POLYSORBATE 60; GLYCERYL STEARATE

PURPOSE

For facial skin moisturizing and nourishing, antioxidant and anti-aging.

INACTIVE INGREDIENT

AQUA，GLYCERIN，PALMITIC ACID，STEARIC ACID，MINERAL OIL，Diethylene Glycol Monoethyl Ether，LAURIC/MYRISTIC/PALMITIC/STEARIC GLYCERIDES，STEARYL ALCOHOL，CERA ALBA，POLYSORBATE 60，GLYCERYL STEARATE，TRIETHANOLAMINE，CETYL ALCOHOL，PHENOXYETHANOL，ALLANTOIN，FRAGRANCE，METHYLPARABEN，TITANIUM DIOXIDE，MYRISTIC ACID，Piper Methysticum Root Extract，ZINC OXIDE，PROPYLPARABEN，XANTHAN GUM，Bisabolol，LAURIC ACID，BUTYLENEGLYCOL， MYRISTYL ALCOHOL，Arachidyl Alcohol，1,2-HEXANEDIOL，Aluminum Hydroxide

Warning.
1、For external use only, avoid contact with eyes when used
2、Keep out of reach of children

INDICATIONS AND USAGE

Wrinkle Improvement: Improves wrinkles by maintaining skin elasticity by sunnving collagen. The skin looks brighter, more elastic and younger.

DOSAGE AND ADMINISTRATION

Recommended to use twice a day: After waking up in the moming, moistunze the skin. After washing your face in the evening, use it again before going to bed.

KEEP OUT OF REACH OF CHILDREN SECTION

Active Ingredients
HYDROLYZED COLLAGEN EXTRACT0.1%
TOCOPHEROL0.1%
Vigna Radiata Seed Extract0.1%

PACKAGE LABEL

Active Ingredients
HYDROLYZED COLLAGEN EXTRACT0.1%
TOCOPHEROL0.1%
Vigna Radiata Seed Extract0.1%

Uses：
For facial skin moisturizing and nourishing, antioxidant and anti-aging.
The storage method：
Store sealed in a cool place and out of sunlight

Warning.
1、For external use only, avoid contact with eyes when used
2、Keep out of reach of children

Inactive ingredients：
AQUA，GLYCERIN，PALMITIC ACID，STEARIC ACID，MINERAL OIL，Diethylene Glycol Monoethyl Ether，LAURIC/MYRISTIC/PALMITIC/STEARIC GLYCERIDES，STEARYL ALCOHOL，CERA ALBA，POLYSORBATE 60，GLYCERYL STEARATE，TRIETHANOLAMINE，CETYL ALCOHOL，PHENOXYETHANOL，ALLANTOIN，FRAGRANCE，METHYLPARABEN，TITANIUM DIOXIDE，MYRISTIC ACID，Piper Methysticum Root Extract，ZINC OXIDE，PROPYLPARABEN，XANTHAN GUM，Bisabolol，LAURIC ACID，BUTYLENEGLYCOL， MYRISTYL ALCOHOL，Arachidyl Alcohol，1,2-HEXANEDIOL，Aluminum Hydroxide